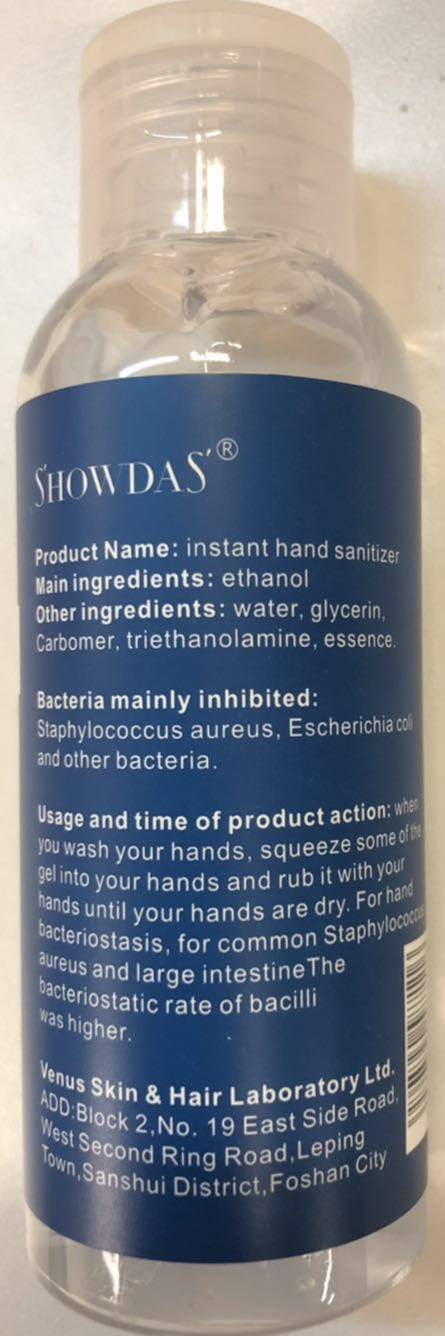 DRUG LABEL: Instant Hand Sanitizer
NDC: 54708-002 | Form: GEL
Manufacturer: Venus Skin & Hair Laboratory Ltd.
Category: otc | Type: HUMAN OTC DRUG LABEL
Date: 20200424

ACTIVE INGREDIENTS: ALCOHOL 68.4 mL/100 mL
INACTIVE INGREDIENTS: TRIETHANOLAMINE CACODYLATE; CARBOMER HOMOPOLYMER, UNSPECIFIED TYPE; WATER; PROPYLENE; GLYCERIN

DOSAGE AND ADMINISTRATION

Do not place this product in high temperature or direct sunlight.

INACTIVE INGREDIENT

water

propylene glycol

glycerin

carbomer triethanolamine

INDICATIONS AND USAGE

when you wash your hands,squeeze some of the gel into your hands and rub it with your hand unitl are dry.

ACTIVE INGREDIENT

ALCOHOL

keep out of children

PURPOSE

Disinfection
Sterilization
No Rinseing

WARNINGS

Do not place this product in high temperature or direct sunlight.keep out of children